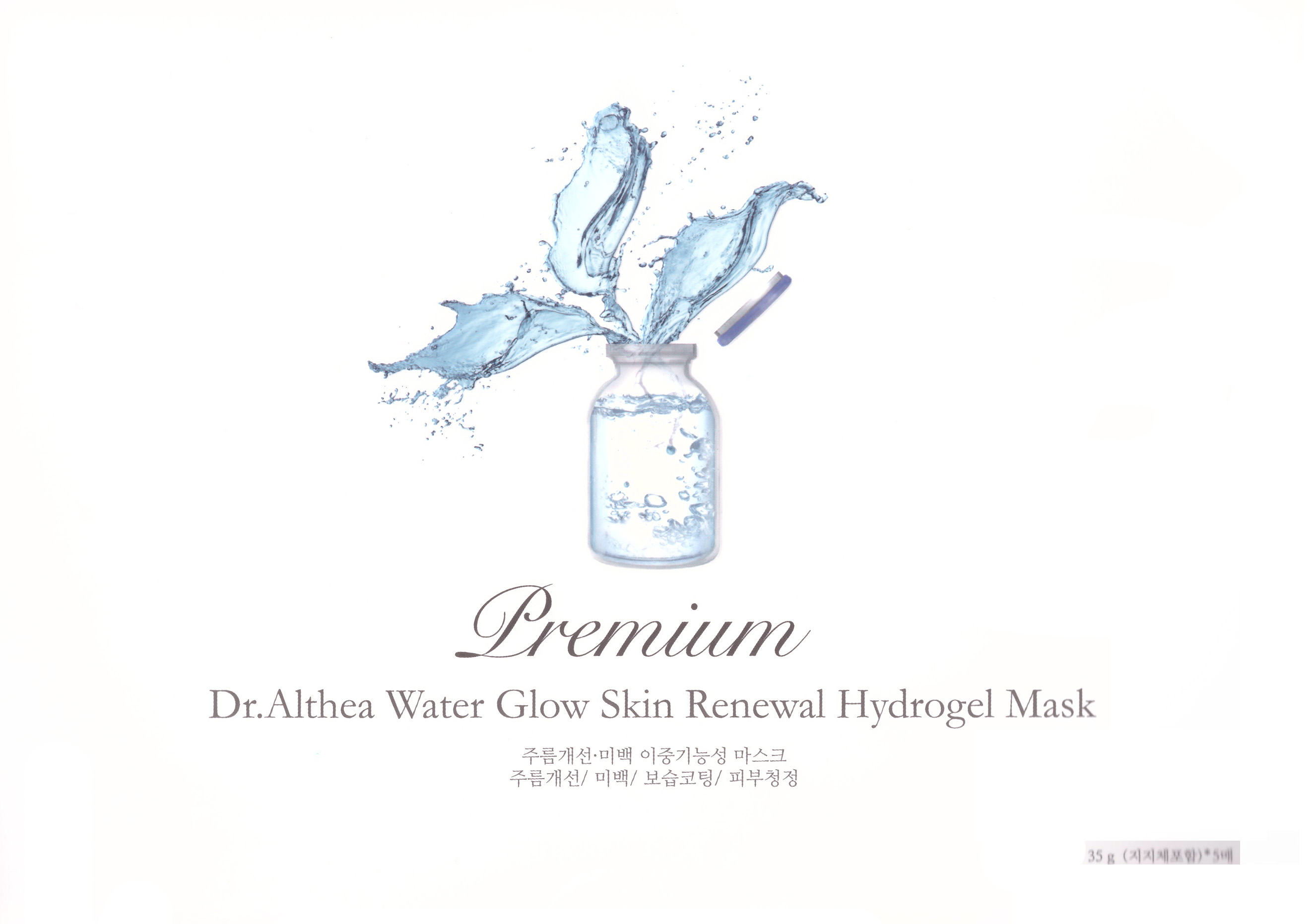 DRUG LABEL: Premium Dr. Althea Water Glow Skin Renewal Hydrogel Mask
NDC: 70905-0006 | Form: LIQUID
Manufacturer: Dr. Althea
Category: otc | Type: HUMAN OTC DRUG LABEL
Date: 20160812

ACTIVE INGREDIENTS: NIACINAMIDE 2 g/100 g; ADENOSINE 0.04 g/100 g
INACTIVE INGREDIENTS: WATER; BUTYLENE GLYCOL

Drug Facts

ACTIVE INGREDIENT

Niacinamide, Adenosine

INACTIVE INGREDIENT

Water, Glycerin, Caprylic/Capric Triglyceride, Ceratonia Siliqua Gum, Polysorbate 60, Chondrus Crisps Powder, Lactobacillus Ferment, Scutellaria Baicalensis Root Extract, Camellia Sinensis Leaf Extract, Artemisia Princeps Leaf Extract, Houttuynia Cordata Extract, Citrus Junos Fruit Extract, Ricans Communis (Castor) Seed Oil, 1,2-Hexanediol, Caprylyl Glycol, Phenoxyethanol, Allantoin, Panthenol, Ethylhexylglycerin, Disodium EDTA, Butylene Glycol, Sodium Hyaluronate, Hydrolyzed Collagen, Bellis Perennis (Daisy) Flower Extract, Lillium Candidum Flower Extract, Mirabilis Jalapa Extract, Sambucus Nigra Flower Extract, Nelunbium Speciosum Flower Extract, Convallaria Majalis Extract, Jasminum Officinale(Jasmine) Flower Extract, Paeonia Albiflora Flower Extract, Lonicera Japonica(Honeysuckle) Flower Extract, Hyacinthus Orientalis(Hyacinth) Flower Extract, Harpagophytum Procumbens Root Extract, Portulaca Oleracea Extract, Agave Americana Leaf Extract, Rhodiola Sacra Root Extract, Vaccinium Vitis-Idaea Leaf Extract, Leontopodium Alpinum Extract, Alcohol, Potassium Hydroxide, Citrus Medica Limonum (Lemon) Peel Oil, Citrus Aurantium Dulcis (Orange) Oil, Geranium Maculatum Oil, Propolis Extract, Snail Secretion Filtrate, Dipotassium Glycyrrhizate, Leucojum Aestivum Bulb Extract, Argania Spinosa Kernel Oil, Simmondsia Chinensis (Jojoba) Seed Oil, Rosa Canina Fruit Oil, Vitis Vinifera (Grape) Seed Oil, Cocos Nucifera (Coconut) Oil

PURPOSE

Helps to fight against wrinkles. Helps skin whitening

keep out of reach of the children

INDICATIONS AND USAGE

Open the pouch and take out a mask. Remove films on the both side and attach to face for 20~40 minutes, then remove the mask.

WARNINGS

1. If the following symptoms occur after product use, stop using the product immediately and consult a dermatologist (continuous use can exacerbate the symptoms).
1) Occurrence of red spots, swelling, itchiness, and other skin irritation
2) If the symptoms above occur after the application area is exposed to direct sunlight
2. Do not use on open wounds, eczema, and other skin irritations
3. Precaution for Storage and Handling
1) Close the lid after use
2) Keep out of reach of infants and children
3) Do not to store in a place with high/low temperature and exposed to direct sunlight

4. Use as avoiding eye areas.

DOSAGE AND ADMINISTRATION

for external use only